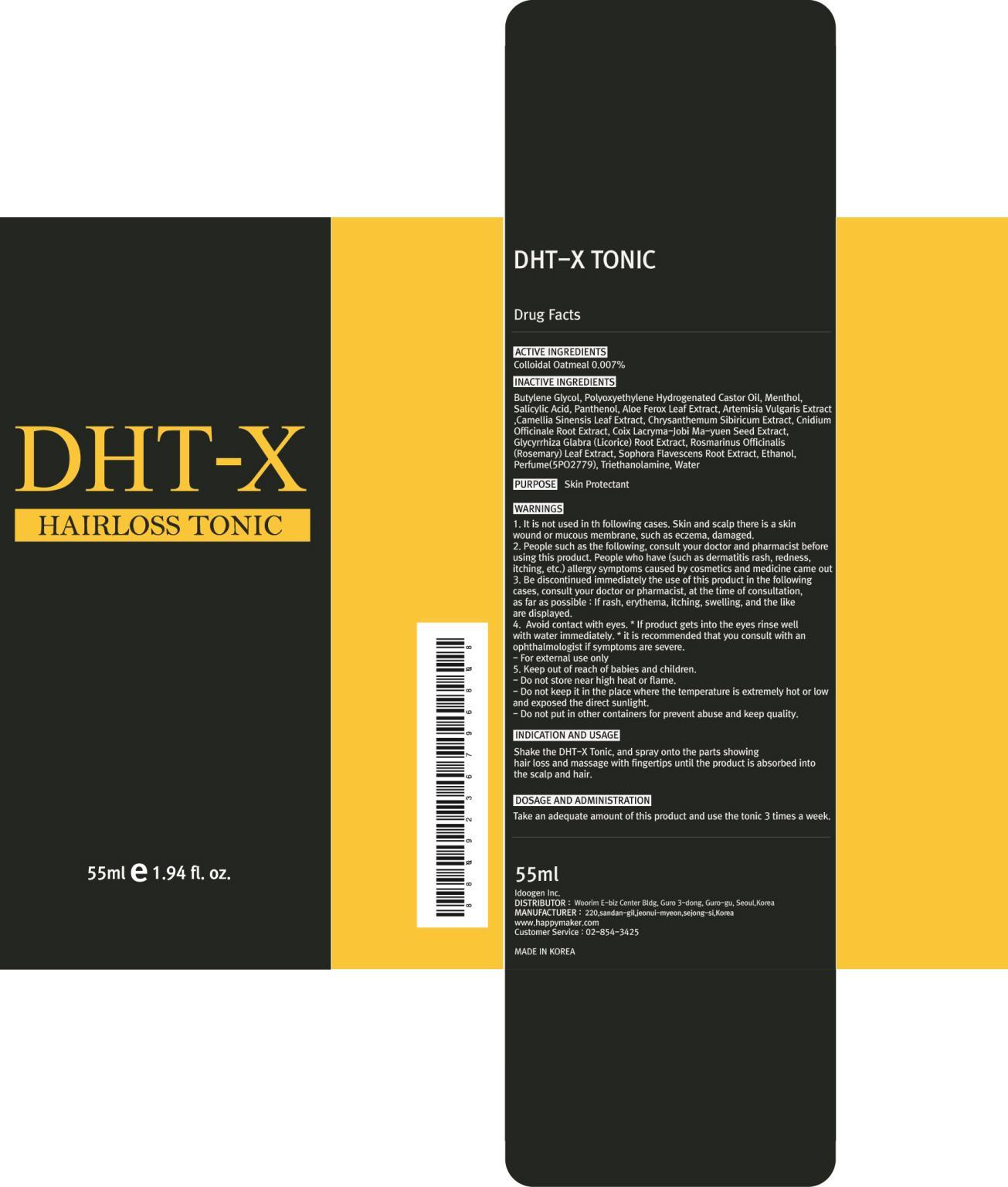 DRUG LABEL: DHT X TONIC
NDC: 69281-010 | Form: SOLUTION
Manufacturer: IDOOGEN CO., LTD.
Category: otc | Type: HUMAN OTC DRUG LABEL
Date: 20141020

ACTIVE INGREDIENTS: OATMEAL 0.003 mg/55 mL
INACTIVE INGREDIENTS: Butylene Glycol; Menthol

ACTIVE INGREDIENT

ACTIVE INGREDIENTS : Colloidal Oatmeal 0.007%

INACTIVE INGREDIENT

INACTIVE INGREDIENTS :
Butylene Glycol, Polyoxyethylene Hydrogenated Castor Oil, Menthol, Salicylic Acid, Panthenol, Aloe Ferox Leaf Extract, Artemisia Vulgaris Extract, Camellia Sinensis Leaf Extract, Chrysanthemum Sibiricum Extract, Cnidium Officinale Root Extract, Coix Lacryma-Jobi Ma-yuen Seed Extract, Glycyrrhiza Glabra (Licorice) Root Extract, Rosmarinus Officinalis (Rosemary) Leaf Extract, Sophora Flavescens Root Extract, Ethanol, Perfume(5PO2779), Triethanolamine, Water

PURPOSE

PURPOSE : Skin Protectant

WARNINGS

1. It is not used in th following cases. Skin and scalp there is a skin wound or mucous membrane, such as eczema, damaged
2. People such as the following, consult your doctor and pharmacist before using this product. People who have (such as dermatitis rash, redness, itching, etc.) allergy symptoms caused by cosmetics and medicine came out
3. Be discontinued immediately the use of this product in the following cases, consult your doctor or pharmacist, at the time of consultation, as far as possible : If rash, erythema, itching, swelling, and the like are displayed
4. Avoid contact with eyes. * If product gets into the eyes rinse well with water immediately. * it is recommended that you consult with an ophthalmologist if symptoms are severe
- For external use only
5. Keep out of reach of babies and children
- Do not store near high heat or flame
- Do not keep it in the place where the temperature is extremely hot or low and exposed the direct sunlight.
- Do not put in other containers for prevent abuse and keep quality

KEEP OUT OF REACH OF CHILDREN

Keep out of reach of babies and children

INDICATIONS & USAGE

INDICATION AND USAGE :
Shake the DHT-X Tonic, and spray onto the parts showing hair loss and massage with fingertips until the product is absorbed into the scalp and hair

DOSAGE & ADMINISTRATION

DOSAGE AND ADMINISTRATION :
Take an adequate amount of this product and use the tonic 3 times a week